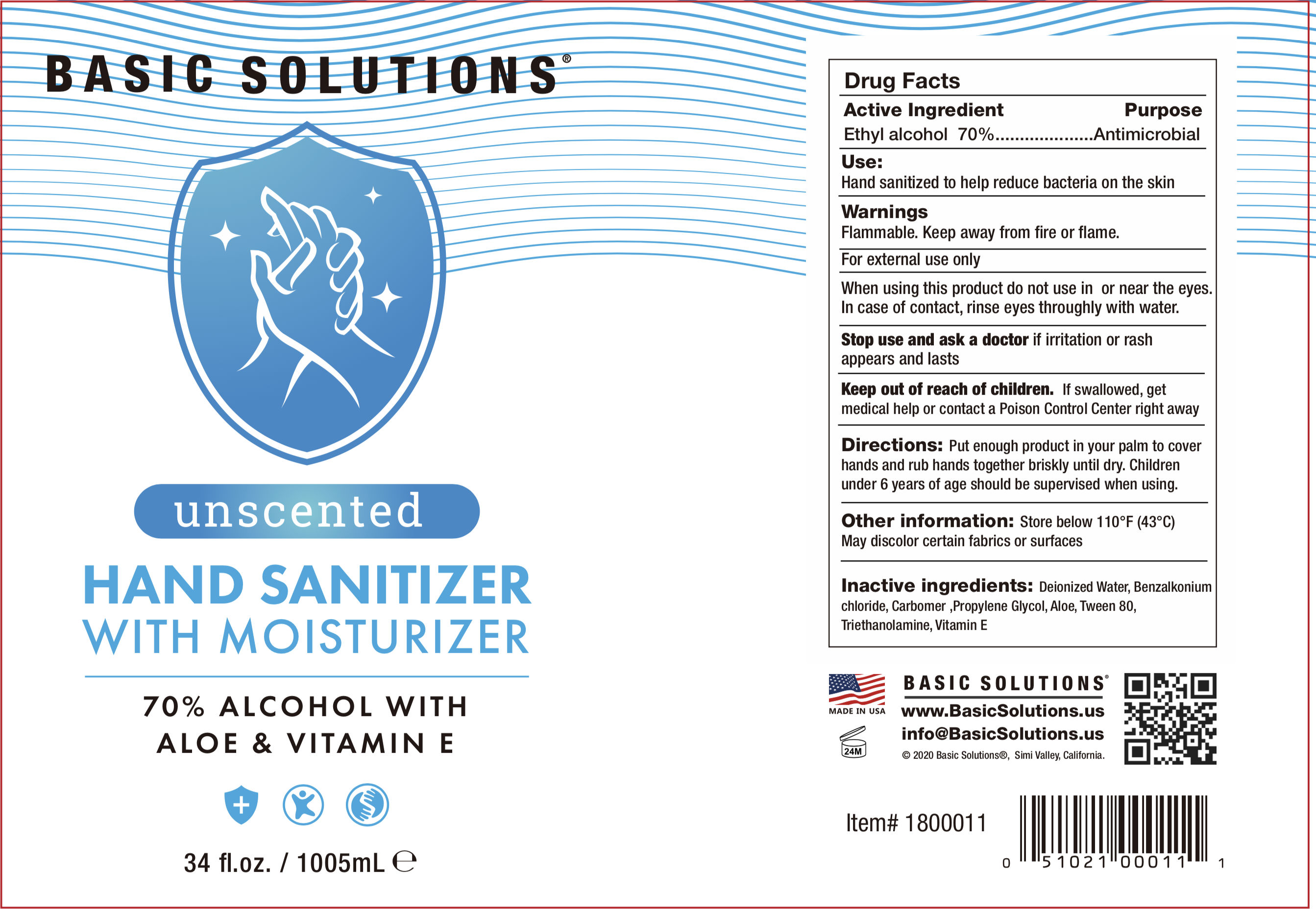 DRUG LABEL: Basic Solutions Hand sanitizer with moisturizer 34 oz unscented
NDC: 69797-008 | Form: GEL
Manufacturer: Wsm Investments, LLC Topco Sales
Category: otc | Type: HUMAN OTC DRUG LABEL
Date: 20200610

ACTIVE INGREDIENTS: ALCOHOL 703.5 mL/1005 mL
INACTIVE INGREDIENTS: PROPYLENE GLYCOL; ALOE; CARBOMER HOMOPOLYMER, UNSPECIFIED TYPE; TROLAMINE; BENZALKONIUM CHLORIDE; WATER; POLYSORBATE 80

DOSAGE AND ADMINISTRATION

Store below 110°F (43°C)

INACTIVE INGREDIENT

Deionized Water、Propylene Glycol、Aloe、Tween 80、Carbomer、Triethanolamine、Benzalkonium chloride

INDICATIONS AND USAGE

Put enough product in your palm to cover hands and ub hands together briskly until dry.

ACTIVE INGREDIENT

Ethyl alcohol

keep out of reach of children

PURPOSE

Disinfection
Sterilization
No Rinseing

WARNINGS

Flammable. Keep away from fire or flame.